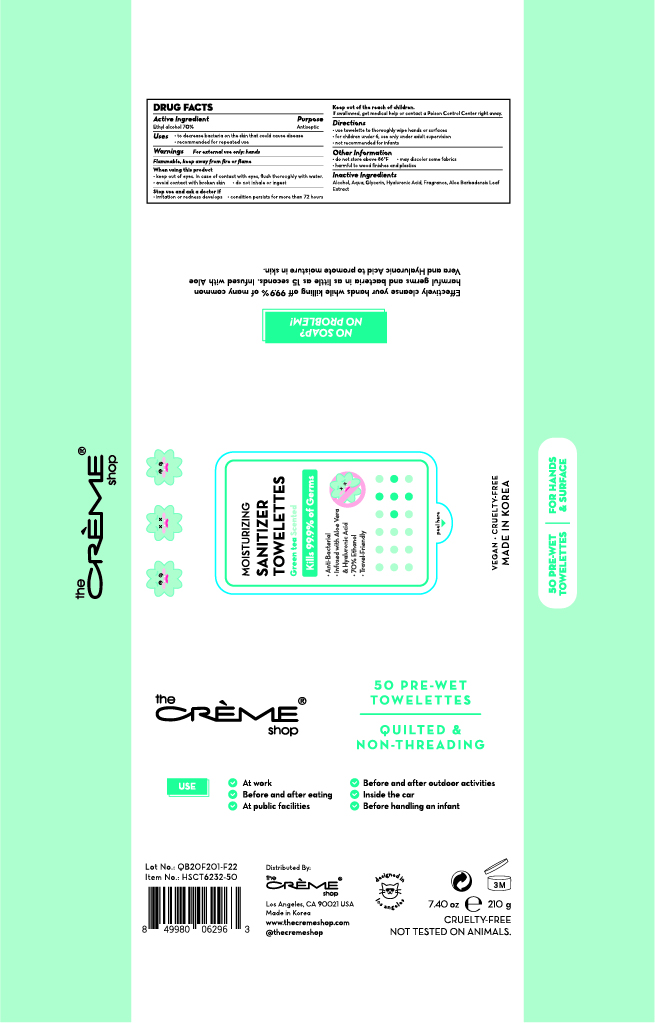 DRUG LABEL: The creme shop Moisturizing Sanitizer Towelettes Green Tea Scented
NDC: 74741-7204 | Form: CLOTH
Manufacturer: MPRBRAIN CO.LTD
Category: otc | Type: HUMAN OTC DRUG LABEL
Date: 20200616

ACTIVE INGREDIENTS: ALCOHOL 0.7 g/1 1
INACTIVE INGREDIENTS: ALOE VERA LEAF; GLYCERIN; HYALURONIC ACID; WATER

The creme shop Moisturizing Sanitizer Towelettes Green Tea Scented : 50 Towelettes
74741-7204-1